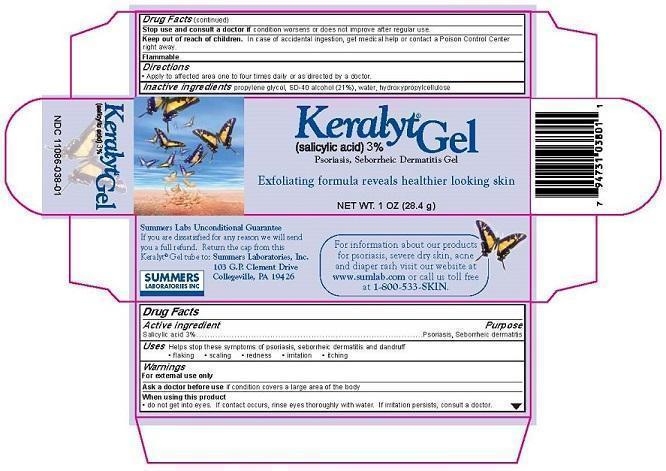 DRUG LABEL: Keralyt
NDC: 11086-038 | Form: GEL
Manufacturer: Summers Laboratories Inc
Category: otc | Type: HUMAN OTC DRUG LABEL
Date: 20231009

ACTIVE INGREDIENTS: SALICYLIC ACID 3 g/100 g
INACTIVE INGREDIENTS: PROPYLENE GLYCOL; ALCOHOL; HYDROXYPROPYL CELLULOSE; WATER

SUMMERS LABS (as PLD) - KERALYT GEL 3% SALICYLIC ACID (11086-038)

ACTIVE INGREDIENT

SALICYLIC ACID 3%

PURPOSE

PSORIASIS, SEBORRHEIC DERMATITIS

USES

HELPS STOP THESE SYMPTOMS OF PSORIASIS, SEBORRHEIC DERMATITIS AND DANDRUFF

- FLAKING
- SCALING
- REDNESS
- IRRITATION
- ITCHING

WARNINGS

FOR EXTERNAL USE ONLY

ASK A DOCTOR BEFORE USE IF CONDITION COVERS A LARGE AREA OF THE BODY

WHEN USING THIS PRODUCT

- DO NOT GET INTO EYES. IF CONTACT OCCURS, RINSE EYES THOROUGHLY WITH WATER. IF IRRITATION PERSISTS, CONSULT A DOCTOR.

STOP USE AND CONSULT A DOCTOR IF CONDITION WORSENS OR DOES NOT IMPROVE AFTER REGULAR USE.

KEEP OUT OF REACH OF CHILDREN. IN CASE OF ACCIDENTAL INGESTION, GET MEDICAL HELP OR CONTACT A POISON CONTROL CENTER RIGHT AWAY.

OTHER SAFETY INFORMATION

FLAMMABLE

DIRECTIONS

- APPLY TO AFFECTED AREA ONE TO FOUR TIMES DAILY OR AS DIRECTED BY A DOCTOR.

INACTIVE INGREDIENTS

PROPYLENE GLYCOL, SD-40 ALCOHOL (21%), WATER, HYDROXYPROPYLCELLULOSE